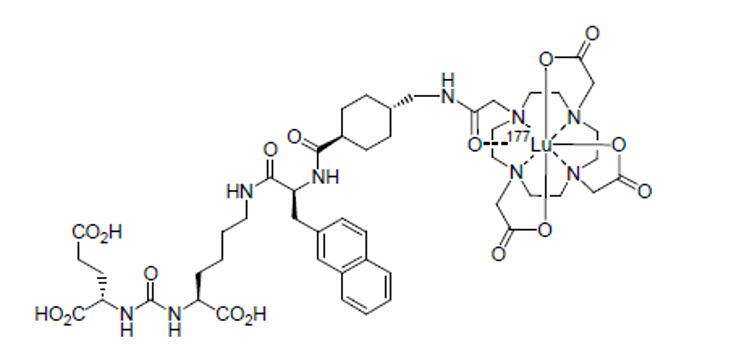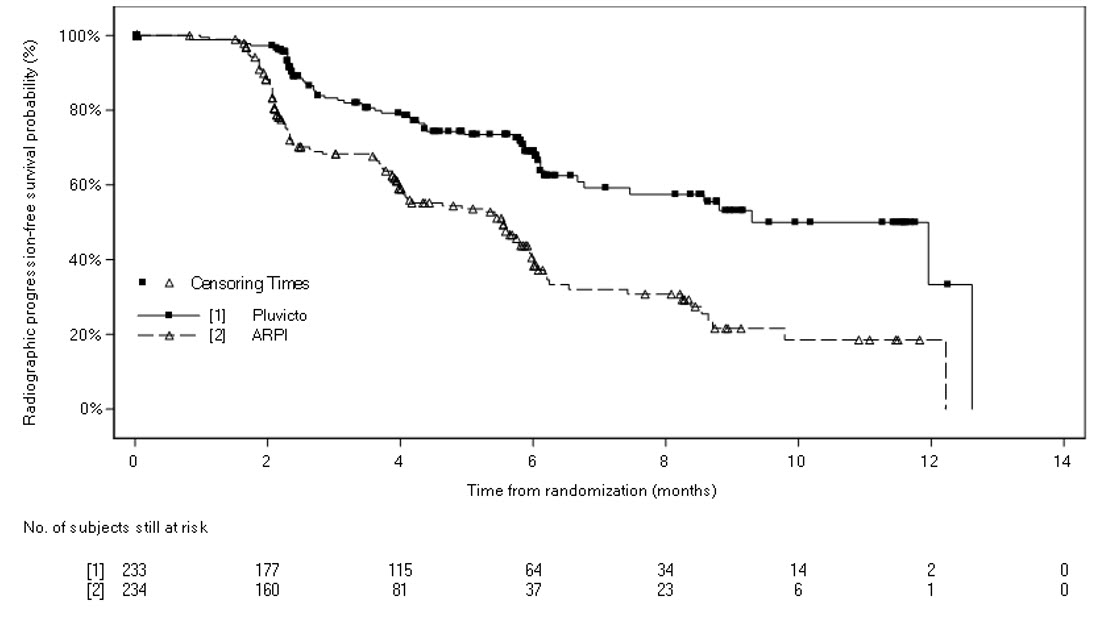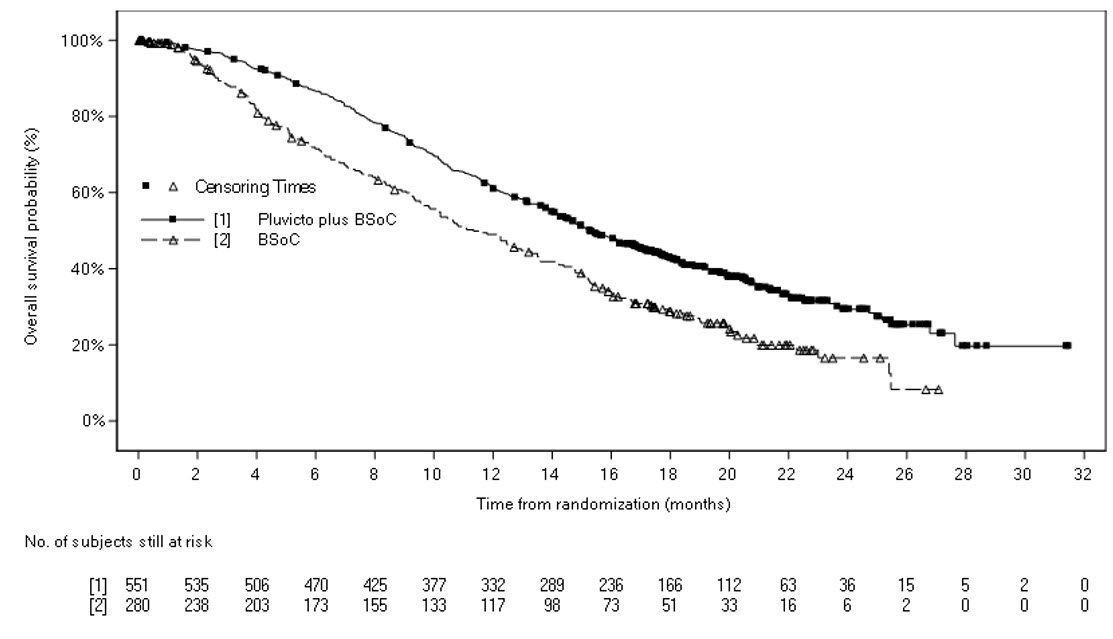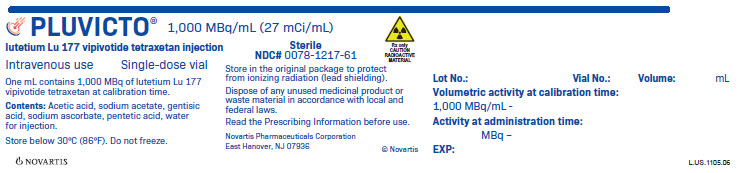 DRUG LABEL: PLUVICTO
NDC: 0078-1217 | Form: INJECTION, SOLUTION
Manufacturer: Novartis Pharmaceuticals Corporation
Category: prescription | Type: HUMAN PRESCRIPTION DRUG LABEL
Date: 20260115

ACTIVE INGREDIENTS: LUTETIUM LU-177 VIPIVOTIDE TETRAXETAN 27 mCi/1 mL
INACTIVE INGREDIENTS: ACETIC ACID; SODIUM ACETATE; GENTISIC ACID; SODIUM ASCORBATE; PENTETIC ACID; WATER

HIGHLIGHTS OF PRESCRIBING INFORMATION

These highlights do not include all the information needed to use PLUVICTO safely and effectively. See full prescribing information for PLUVICTO.
PLUVICTO® (lutetium Lu 177 vipivotide tetraxetan) injection, for intravenous use
Initial U.S. Approval: 2022

RECENT MAJOR CHANGES

Indications and Usage (1) | 3/2025
Dosage and Administration, Patient Selection (2.2) | 3/2025
Dosage and Administration, Preparation and Administration (2.5) | 3/2025
Warnings and Precautions, Myelosuppression (5.2) | 3/2025
Warnings and Precautions, Renal Toxicity (5.3) | 3/2025

1 INDICATIONS AND USAGE

PLUVICTO is a radioligand therapeutic agent indicated for the treatment of adult patients with prostate-specific membrane antigen (PSMA)-positive metastatic castration-resistant prostate cancer (mCRPC) who have been treated with androgen receptor pathway inhibitor (ARPI) therapy, and

- are considered appropriate to delay taxane-based chemotherapy, or
- have received prior taxane-based chemotherapy. (1)

2 DOSAGE AND ADMINISTRATION

- Select patients for treatment using LOCAMETZ® or another approved PSMA positron emission tomography (PET) product based on PSMA expression in tumors. (2.2)
- Recommended Dosage: Administer 7.4 GBq (200 mCi) every 6 weeks for 6 doses. (2.3)
- Dose interruption, reduction, or permanent discontinuation may be required due to adverse reactions. (2.4)

3 DOSAGE FORMS AND STRENGTHS

Injection: 1,000 MBq/mL (27 mCi/mL) in a single-dose vial. (3)

4 CONTRAINDICATIONS

None. (4)

5 WARNINGS AND PRECAUTIONS

- Risk From Radiation Exposure: Minimize radiation exposure during and after treatment with PLUVICTO consistent with institutional good radiation safety practices and patient treatment procedures. Ensure patients increase oral fluid intake and advise patients to void as often as possible to reduce bladder radiation. (5.1)
- Myelosuppression: Perform complete blood counts. Withhold, reduce dose, or permanently discontinue PLUVICTO based on severity. (2.4, 5.2)
- Renal Toxicity: Advise patients to remain well hydrated and to urinate frequently. Perform kidney function laboratory tests. Withhold, reduce dose, or permanently discontinue PLUVICTO based on severity. (2.4, 5.3)
- Embryo-Fetal Toxicity: Can cause fetal harm. Advise males with female partners of reproductive potential to use effective contraception. (5.4, 8.1, 8.3)
- Infertility: PLUVICTO may cause temporary or permanent infertility. (5.5, 8.3)

6 ADVERSE REACTIONS

Most common (≥ 20%) adverse reactions, including laboratory abnormalities, were decreased lymphocytes, decreased hemoglobin, fatigue, dry mouth, decreased platelets, decreased estimated glomerular filtration rate, nausea, decreased neutrophils, decreased calcium, decreased sodium, increased aspartate aminotransferase, increased alkaline phosphatase, arthralgia, decreased appetite, increased potassium, constipation, and back pain. (6.1)

To report SUSPECTED ADVERSE REACTIONS, contact Novartis Pharmaceuticals Corporation at 1-888-669-6682 or FDA at 1-800-FDA-1088 or www.fda.gov/medwatch.

FULL PRESCRIBING INFORMATION

1 INDICATIONS AND USAGE

PLUVICTO is indicated for the treatment of adult patients with prostate-specific membrane antigen (PSMA)-positive metastatic castration-resistant prostate cancer (mCRPC) who have been treated with androgen receptor pathway inhibitor (ARPI) therapy, and

- are considered appropriate to delay taxane-based chemotherapy, or
- have received prior taxane-based chemotherapy.

2 DOSAGE AND ADMINISTRATION

2.1 Important Safety Instructions

PLUVICTO is a radiopharmaceutical; handle with appropriate safety measures to minimize radiation exposure [see Warnings and Precautions (5.1)]. Use waterproof gloves and effective radiation shielding when handling PLUVICTO.

Radiopharmaceuticals, including PLUVICTO, should be used by or under the control of healthcare providers who are qualified by specific training and experience in the safe use and handling of radiopharmaceuticals, and whose experience and training have been approved by the appropriate governmental agency authorized to license the use of radiopharmaceuticals.

2.2 Patient Selection

Select patients with previously treated mCRPC for treatment with PLUVICTO using LOCAMETZ or another approved PSMA positron emission tomography (PET) product based on PSMA expression in tumors. Additional selection criteria were used in clinical studies [see Clinical Studies (14)].

2.3 Recommended Dosage

The recommended PLUVICTO dosage is 7.4 GBq (200 mCi) intravenously every 6 weeks for 6 doses, or until disease progression, or unacceptable toxicity.

2.4 Dosage Modifications for Adverse Reactions

Recommended dosage modifications of PLUVICTO for adverse reactions are provided in Table 1. Management of adverse reactions may require temporary dose interruption, dose reduction or permanent discontinuation of treatment with PLUVICTO. If a treatment delay due to an adverse reaction persists for > 4 weeks, consider permanent discontinuation of PLUVICTO. The dose of PLUVICTO may be reduced by 20% to 5.9 GBq (160 mCi) once; do not re-escalate dose. If a patient has further adverse reactions that would require an additional dose reduction, treatment with PLUVICTO must be discontinued.

Table 1: Recommended Dosage Modifications of PLUVICTO for Adverse Reactions
Adverse reaction | Severity | Dosage modification
Myelosuppression (Anemia, thrombocytopenia, leukopenia, or neutropenia) [see Warnings and Precautions (5.2)] | Grade 2 | Withhold PLUVICTO until improvement to Grade 1 or baseline.
 | Grade ≥ 3 | Withhold PLUVICTO until improvement to Grade 1 or baseline. Reduce PLUVICTO dose by 20% to 5.9 GBq (160 mCi).
 | Recurrent Grade ≥ 3 myelosuppression after one dose reduction | Permanently discontinue PLUVICTO.
Renal toxicity [see Warnings and Precautions (5.3)] | Defined as:; - Confirmed serum creatinine increase (Grade ≥ 2) - Confirmed CLcr < 30 mL/min; calculate using Cockcroft-Gault with actual body weight | Withhold PLUVICTO until improvement.
 | Defined as:; - Confirmed ≥ 40% increase from baseline serum creatinine and - Confirmed > 40% decrease from baseline CLcr; calculate using Cockcroft-Gault with actual body weight | Withhold PLUVICTO until improvement or return to baseline. Reduce PLUVICTO dose by 20% to 5.9 GBq (160 mCi).
 | Grade ≥ 3 renal toxicity | Permanently discontinue PLUVICTO.
 | Recurrent renal toxicity after one dose reduction | Permanently discontinue PLUVICTO.
Dry mouth [see Adverse Reactions (6.1)] | Grade 2 | Withhold PLUVICTO until improvement or return to baseline. Consider reducing PLUVICTO dose by 20% to 5.9 GBq (160 mCi).
 | Grade 3 | Withhold PLUVICTO until improvement or return to baseline. Reduce PLUVICTO dose by 20% to 5.9 GBq (160 mCi).
 | Recurrent Grade 3 dry mouth after one dose reduction | Permanently discontinue PLUVICTO.
Gastrointestinal toxicity [see Adverse Reactions (6.1)] | Grade ≥ 3 (not amenable to medical intervention) | Withhold PLUVICTO until improvement to Grade 2 or baseline. Reduce PLUVICTO dose by 20% to 5.9 GBq (160 mCi).
 | Recurrent Grade ≥ 3 gastrointestinal toxicity after one dose reduction | Permanently discontinue PLUVICTO.
Fatigue [see Adverse Reactions (6.1)] | Grade ≥ 3 | Withhold PLUVICTO until improvement to Grade 2 or baseline.
Electrolyte or metabolic abnormalities [see Adverse Reactions (6.1)] | Grade ≥ 2 | Withhold PLUVICTO until improvement to Grade 1 or baseline.
Other non-hematologic toxicity [see Adverse Reactions (6.1)] | Any unacceptable toxicity | Permanently discontinue PLUVICTO.
 | Any adverse reaction that requires treatment delay of > 4 weeks | Permanently discontinue PLUVICTO.
 | Any recurrent Grade 3 or 4 or persistent and intolerable Grade 2 adverse reaction after one dose reduction | Permanently discontinue PLUVICTO.
Abbreviations: CLcr, creatinine clearance; AST, aspartate aminotransferase; ALT, alanine aminotransferase; ULN, upper limit of normal.
Grading according to most current Common Terminology Criteria for Adverse Events (CTCAE).

2.5 Preparation and Administration

Preparation Instructions

- Use aseptic technique and radiation shielding when handling or administering PLUVICTO, using tongs as needed to minimize radiation exposure.
- Inspect the product visually under a shielded screen for particulate matter and discoloration prior to administration. Discard the vial if particulates and/or discoloration are present.
- Do not inject the PLUVICTO solution directly into any other intravenous solution.
- Confirm the amount of radioactivity of PLUVICTO delivered to the patient with an appropriately calibrated dose calibrator prior to and after each PLUVICTO administration.
- Dispose of any unused medicinal product or waste material in accordance with local and federal laws.

Administration Instructions

Prior to administration, flush the intravenous catheter used exclusively for PLUVICTO administration with ≥ 10 mL of 0.9% Sodium Chloride Injection, USP to ensure patency and to minimize the risk of extravasation. Manage cases of extravasation as per institutional guidelines.

The recommended dosage of PLUVICTO may be administered intravenously as an injection using the syringe method, as an infusion using the gravity method, or as an infusion using the peristaltic pump method.

When using the gravity or peristaltic pump method, infuse PLUVICTO directly from its original container.

Use the syringe method or the peristaltic pump method when administering a reduced dose of PLUVICTO following a dosage modification for an adverse reaction. When using the gravity method for a reduced dose, adjust the PLUVICTO dose before the administration to avoid the delivery of an incorrect volume of PLUVICTO.

Intravenous Methods of Administration

Instructions for the Syringe Method

- Withdraw an appropriate volume of PLUVICTO solution to deliver the desired radioactivity by using a disposable syringe fitted with a syringe shield and a disposable sterile needle that is 9 cm, 18 gauge (long needle). To aid the withdrawal of the solution, a filtered 2.5 cm, 20 gauge needle (short venting needle) can be used to reduce the resistance from the pressurized vial. Ensure that the short needle does not touch the PLUVICTO solution in the vial.
- Administer PLUVICTO to the patient by slow intravenous push within approximately 1 to 10 minutes (either with a syringe pump or manually without a syringe pump) via an intravenous catheter that is primed with 0.9% Sodium Chloride Injection, USP and that is used exclusively for PLUVICTO administration to the patient.
- If using a syringe pump, fit the syringe into the shielded pump and include a 3-way stopcock valve between the syringe and an intravenous catheter primed with 0.9% Sodium Chloride Injection, USP and used for PLUVICTO administration to the patient.
- When the desired PLUVICTO radioactivity has been delivered, stop the syringe pump and then change the position of the 3-way stopcock valve to flush the syringe with 25 mL of 0.9% Sodium Chloride Injection, USP. Restart the syringe pump.
- After the flush of the syringe has been completed, perform an intravenous flush of ≥ 10 mL of 0.9% Sodium Chloride Injection, USP through the intravenous catheter to the patient.

Instructions for the Gravity Method

- Insert a 2.5 cm, 20 gauge needle (short needle) into the PLUVICTO vial and connect via a catheter to 500 mL 0.9% Sodium Chloride Injection, USP (used to transport the PLUVICTO solution during the infusion). Ensure that the short needle does not touch the PLUVICTO solution in the vial and do not connect the short needle directly to the patient. Do not allow the 0.9% Sodium Chloride Injection, USP to flow into the PLUVICTO vial prior to the initiation of the PLUVICTO infusion and do not inject the PLUVICTO solution directly into the 0.9% Sodium Chloride Injection, USP.
- Insert a second needle that is 9 cm, 18 gauge (long needle) into the PLUVICTO vial, ensuring that the long needle touches and is secured to the bottom of the PLUVICTO vial during the entire infusion. Connect the long needle to the patient by an intravenous catheter that is primed with 0.9% Sodium Chloride Injection, USP and that is used exclusively for the PLUVICTO infusion into the patient.
- Use a clamp or an infusion pump to regulate the flow of the 0.9% Sodium Chloride Injection, USP via the short needle into the PLUVICTO vial (the 0.9% Sodium Chloride Injection, USP entering the vial through the short needle will carry the PLUVICTO solution from the vial to the patient via the intravenous catheter connected to the long needle within approximately 30 minutes).
- During the infusion, ensure that the level of solution in the PLUVICTO vial remains constant.
- Disconnect the vial from the long needle line and clamp the 0.9% Sodium Chloride Injection, USP line once the level of radioactivity is stable for at least five minutes.
- Follow the infusion with an intravenous flush of ≥ 10 mL of 0.9% Sodium Chloride Injection, USP through the intravenous catheter to the patient.

Instructions for the Peristaltic Pump Method

- Insert a filtered 2.5 cm, 20 gauge needle (short venting needle) into the PLUVICTO vial. Ensure that the short needle does not touch the PLUVICTO solution in the vial and do not connect the short needle directly to the patient or to the peristaltic pump.
- Insert a second needle that is 9 cm, 18 gauge (long needle) into the PLUVICTO vial, ensuring that the long needle touches and is secured to the bottom of the PLUVICTO vial during the entire infusion. Connect the long needle and a 0.9% Sodium Chloride Injection, USP to a 3-way stopcock valve via appropriate tubing.
- Connect the output of the 3-way stopcock valve to tubing installed on the input side of the peristaltic pump according to manufacturer’s instructions.
- Prime the line by opening the 3-way stopcock valve and pumping the PLUVICTO solution through the tubing until it reaches the exit of the valve.
- Prime the intravenous catheter which will be connected to the patient by opening the 3-way stopcock valve to the 0.9% Sodium Chloride Injection, USP and pumping the 0.9% Sodium Chloride Injection, USP until it exits the end of the catheter tubing.
- Connect the primed intravenous catheter to the patient and set the 3-way stopcock valve such that the PLUVICTO solution is in line with the peristaltic pump.
- Infuse an appropriate volume of PLUVICTO solution at approximately 25 mL/h to deliver the desired radioactivity.
- When the desired PLUVICTO radioactivity has been delivered, stop the peristaltic pump and then change the position of the 3-way stopcock valve so that the peristaltic pump is in line with the 0.9% Sodium Chloride Injection, USP. Restart the peristaltic pump and infuse an intravenous flush of ≥ 10 mL of 0.9% Sodium Chloride Injection, USP through the intravenous catheter to the patient.

2.6 Radiation Dosimetry

Dosimetry of lutetium Lu 177 vipivotide tetraxetan was collected in 29 patients in the VISION sub-study, in order to calculate whole body and organ radiation dosimetry. The mean and standard deviation (SD) of the estimated radiation absorbed doses to different organs for adults receiving PLUVICTO are shown in Table 2. The organs with the highest radiation absorbed doses are lacrimal glands, salivary glands, large intestine (left and right colon), kidneys, and urinary bladder wall. The maximum penetration of lutetium-177 in tissue is approximately 2 mm and the mean penetration is 0.67 mm.

Table 2: Estimated Radiation Absorbed Dosea for PLUVICTO in VISION
 | Absorbed dose per unit activity (Gy/GBq) N = 29 |  | Calculated absorbed dose for 7.4 GBq administration (Gy) |  | Calculated absorbed dose for 6 x 7.4 GBq (44.4 GBq cumulative activity) (Gy)
Organ* | Mean | SD | Mean | SD | Mean | SD
Adrenals | 0.033 | 0.025 | 0.24 | 0.19 | 1.5 | 1.1
Brain | 0.007 | 0.005 | 0.049 | 0.035 | 0.30 | 0.22
Esophagus | 0.025 | 0.026 | 0.18 | 0.19 | 1.1 | 1.1
Eyes | 0.022 | 0.024 | 0.16 | 0.18 | 0.99 | 1.1
Gallbladder wall | 0.028 | 0.026 | 0.20 | 0.19 | 1.2 | 1.1
Heart wall | 0.17 | 0.12 | 1.2 | 0.83 | 7.8 | 5.2
Kidneys | 0.43 | 0.16 | 3.1 | 1.2 | 19 | 7.3
Lacrimal glands | 2.1 | 0.47 | 15 | 3.4 | 92 | 21
Left colon | 0.58 | 0.14 | 4.1 | 1.0 | 26 | 6.0
Liver | 0.090 | 0.044 | 0.64 | 0.32 | 4.0 | 2.0
Lungs | 0.11 | 0.11 | 0.76 | 0.81 | 4.7 | 4.9
Pancreas | 0.027 | 0.026 | 0.19 | 0.19 | 1.2 | 1.1
Prostate | 0.027 | 0.026 | 0.19 | 0.19 | 1.2 | 1.1
Rectum | 0.56 | 0.14 | 4.0 | 1.1 | 25 | 6.2
Right colon | 0.32 | 0.078 | 2.3 | 0.58 | 14 | 3.4
Salivary glands | 0.63 | 0.36 | 4.5 | 2.6 | 28 | 16
Small intestine | 0.071 | 0.031 | 0.50 | 0.23 | 3.1 | 1.4
Spleen | 0.067 | 0.027 | 0.48 | 0.20 | 3.0 | 1.2
Stomach wall | 0.025 | 0.026 | 0.18 | 0.19 | 1.1 | 1.1
Testes | 0.023 | 0.025 | 0.16 | 0.18 | 1.0 | 1.1
Thymus | 0.025 | 0.026 | 0.18 | 0.19 | 1.1 | 1.1
Thyroid | 0.26 | 0.37 | 1.8 | 2.7 | 11 | 16
Total body | 0.037 | 0.027 | 0.27 | 0.20 | 1.6 | 1.2
Urinary bladder wall | 0.32 | 0.025 | 2.3 | 0.19 | 14 | 1.1
aRadiation absorbed dose estimates were derived using OLINDA v2.2 radiation dosimetry software, using measured time-activity data from patient imaging as input.
*Estimated radiation absorbed dose for bone marrow is not included given the wide expected variability based on location and burden of bone metastases between patients [see Warnings and Precautions (5.2)].

3 DOSAGE FORMS AND STRENGTHS

Injection: 1,000 MBq/mL (27 mCi/mL) of lutetium Lu 177 vipivotide tetraxetan as a clear and colorless to slightly yellow solution in a single-dose vial.

4 CONTRAINDICATIONS

None.

5 WARNINGS AND PRECAUTIONS

5.1 Risk From Radiation Exposure

PLUVICTO contributes to a patient’s overall long-term cumulative radiation exposure. Long-term cumulative radiation exposure is associated with an increased risk for cancer.

Minimize radiation exposure to patients, medical personnel, and others during and after treatment with PLUVICTO consistent with institutional good radiation safety practices, patient treatment procedures, Nuclear Regulatory Commission patient-release guidance, and instructions to the patient for follow-up radiation protection at home.

Ensure patients increase oral fluid intake and advise patients to void as often as possible to reduce bladder radiation.

Before the patient is released, inform patients about the necessary radioprotection precautions to follow to minimize radiation exposure to others [see Patient Counseling Information (17)].

After each administration of PLUVICTO, advise patients to:

- Limit close contact (less than 3 feet) with others for 2 days or with children and pregnant women for 7 days.
- Refrain from sexual activity for 7 days.
- Sleep in a separate room from others for 3 days, from children for 7 days, or from pregnant women for 15 days.

5.2 Myelosuppression

PLUVICTO can cause severe and life-threatening myelosuppression, including anemia, thrombocytopenia, leukopenia, and neutropenia.

In the PSMAfore study, Grade 3 or 4 decreased hemoglobin (7%), decreased leukocytes (4.4%), decreased neutrophils (3.5%), and decreased platelets (2.7%) occurred in patients treated with PLUVICTO. One death occurred due to bone marrow failure during long-term follow-up in a patient who received PLUVICTO.

In the VISION study, Grade 3 or 4 decreased hemoglobin (15%), decreased platelets (9%), decreased leukocytes (7%), and decreased neutrophils (4.5%) occurred in patients treated with PLUVICTO. Grade ≥ 3 pancytopenia occurred in 1.1% (which includes two fatal events) of patients treated with PLUVICTO. Two deaths (0.4%) occurred due to intracranial hemorrhage and subdural hematoma in association with thrombocytopenia, one death (0.2%) occurred due to sepsis and concurrent neutropenia, and one death (0.2%) occurred due to bone marrow failure.

Perform complete blood counts before and during treatment with PLUVICTO. Withhold, reduce dose, or permanently discontinue PLUVICTO based on the severity of myelosuppression [see Dosage and Administration (2.4)].

5.3 Renal Toxicity

PLUVICTO can cause severe renal toxicity.

In the PSMAfore study, Grade 3 or 4 acute kidney injury (1.3%) occurred in patients treated with PLUVICTO. In the VISION study, Grade 3 or 4 acute kidney injury (3.4%) occurred in patients treated with PLUVICTO.

Advise patients to remain well hydrated and to urinate frequently before and after administration of PLUVICTO. Perform kidney function laboratory tests, including serum creatinine and calculated creatinine clearance (CLcr), before and during treatment with PLUVICTO. Withhold, reduce dose, or permanently discontinue PLUVICTO based on the severity of renal toxicity [see Dosage and Administration (2.4)].

5.4 Embryo-Fetal Toxicity

The safety and efficacy of PLUVICTO have not been established in females. Based on its mechanism of action, PLUVICTO can cause fetal harm [see Clinical Pharmacology (12.1)]. No animal studies using lutetium Lu 177 vipivotide tetraxetan have been conducted to evaluate its effect on female reproduction and embryo-fetal development; however, radioactive emissions, including those from PLUVICTO, can cause fetal harm. Advise males with female partners of reproductive potential to use effective contraception during treatment with PLUVICTO and for 14 weeks after the last dose [see Use in Specific Populations (8.1, 8.3)].

5.5 Infertility

PLUVICTO may cause infertility in males. The recommended cumulative dose of 44.4 GBq of PLUVICTO results in a radiation absorbed dose to the testes within the range where PLUVICTO may cause temporary or permanent infertility [see Use in Specific Populations (8.3)].

6 ADVERSE REACTIONS

The following clinically significant adverse reactions are described elsewhere in the labeling:

- Myelosuppression [see Warnings and Precautions (5.2)]
- Renal Toxicity [see Warnings and Precautions (5.3)]

6.1 Clinical Trials Experience

Because clinical trials are conducted under widely varying conditions, adverse reaction rates observed in the clinical trials of a drug cannot be directly compared to rates in the clinical trials of another drug and may not reflect the rates observed in practice.

In the pooled safety population for the PSMAfore and VISION studies (N = 756), the most common (≥ 20%) adverse reactions, including laboratory abnormalities, were decreased lymphocytes (83%), decreased hemoglobin (65%), fatigue (49%), dry mouth (46%), decreased platelets (40%), decreased estimated glomerular filtration rate (37%), nausea (35%), decreased neutrophils (31%), decreased calcium (29%), decreased sodium (27%), increased aspartate aminotransferase (26%), increased alkaline phosphatase (24%), arthralgia (22%), decreased appetite (21%), increased potassium (21%), constipation (21%), and back pain (21%).

PSMAfore

The safety of PLUVICTO was evaluated in the PSMAfore study in patients with progressive, PSMA-positive mCRPC previously treated with ARPI therapy, for whom it was considered appropriate to delay taxane-based chemotherapy by the investigator [see Clinical Studies (14.1)]. Patients received at least one dose of either PLUVICTO 7.4 GBq (200 mCi) administered every 6 weeks (N = 227) or a change in ARPI (N = 232). The median duration of exposure to PLUVICTO was 8.4 months (range, 0.4 to 11.6), and the median number of doses of PLUVICTO received was 6 (range, 1 to 6). The median cumulative administered activity of PLUVICTO was 42.4 GBq (range, 7.0 to 45.4).

Serious adverse reactions occurred in 20% of patients who received PLUVICTO. Serious adverse reactions in > 1% of patients who received PLUVICTO included anemia (1.8%), urinary tract infection (1.8%), hemorrhage (1.3%), and sepsis (1.3%).

Fatal adverse reactions occurred in 1.8% of patients who received PLUVICTO, including COVID-19 pneumonia, cardiac arrest, intestinal ischemia, and sepsis (0.4% each).

PLUVICTO was permanently discontinued due to adverse reactions in 6% of patients. Adverse reactions leading to permanent discontinuation of PLUVICTO in ≥ 1% of patients who received PLUVICTO were thrombocytopenia (1.8%) and dry mouth (1.3%).

Adverse reactions leading to a dose interruption of PLUVICTO occurred in 12% of patients. The most frequent (≥ 1%) adverse reactions leading to a dose interruption of PLUVICTO in patients who received PLUVICTO were COVID-19 (3.1%) and anemia (1.8%).

Adverse reactions leading to a dose reduction of PLUVICTO occurred in 3.5% of patients. The most frequent (≥ 0.5%) adverse reaction leading to a dose reduction of PLUVICTO in patients who received PLUVICTO was dry mouth (0.9%).

Table 3 and Table 4 summarize the incidence of adverse reactions and laboratory abnormalities, respectively, in PSMAfore.

Table 3: Adverse Reactions (≥ 10%) in Patients With PSMA-Positive mCRPC Who Received PLUVICTO in PSMAfore
Adverse reactions | PLUVICTO (N = 227) |  | ARPI (N = 232)
Adverse reactions | All Grades (%) | Grades 3 or 4 (%) | All Grades (%) | Grades 3 or 4 (%)
Gastrointestinal disorders
Dry moutha | 61 | 0.9 | 2.6 | 0
Nausea | 32 | 0 | 12 | 0.4
Constipation | 22 | 0.4 | 14 | 0
Diarrhea | 17 | 0 | 9 | 0.4
Vomiting | 11 | 0 | 4.7 | 0
General disorders
Fatiguea | 53 | 1.3 | 53 | 5
Metabolism and nutrition disorders
Decreased appetite | 22 | 0 | 19 | 0.4
Musculoskeletal and connective tissue disorders
Arthralgia | 20 | 0 | 23 | 0.4
Back pain | 14 | 1.3 | 20 | 2.6
Abbreviation: ARPI, androgen receptor pathway inhibitor.
aIncludes multiple similar terms.

Clinically relevant adverse reactions in < 10% of patients who received PLUVICTO included dysgeusia, abdominal pain, peripheral edema, headache, acute kidney injury, weight decreased, urinary tract infection, dry eye, dizziness, dry skin, oral fungal infection, gastroesophageal reflux disease, pyrexia, vertigo, stomatitis, dysphagia, esophagitis, pancytopenia, and bone marrow failure.

Table 4: Select Laboratory Abnormalities (≥ 10%) That Worsened From Baseline in Patients With PSMA-Positive mCRPC Who Received PLUVICTO or Change in ARPI (Between Arm Difference of ≥ 5% All Grades) in PSMAfore
Laboratory abnormalities | PLUVICTOa |  | ARPIb
Laboratory abnormalities | All Grades (%) | Grades 3 or 4 (%) | All Grades (%) | Grades 3 or 4 (%)
Hematology
Decreased lymphocytes | 78 | 27 | 57 | 12
Decreased hemoglobin | 67 | 7c | 50 | 7c
Decreased neutrophils | 38 | 3.5 | 18 | 1.3
Decreased platelets | 30 | 2.7 | 11 | 1.7
Chemistry
Increased alkaline phosphatase | 31 | 8 | 50 | 10c
Decreased estimated glomerular filtration rate (eGFR) | 23 | 0.9c | 22 | 3.5
Increased magnesium | 19 | 0.9c | 28 | 0c
Decreased calcium | 18 | 0.9 | 11 | 0.9
Decreased sodium | 11 | 0c | 18 | 0c
Decreased potassium | 6 | 0.9c | 18 | 2.6
Abbreviation: ARPI, androgen receptor pathway inhibitor.
aThe denominator used to calculate the rate for each laboratory parameter was based on 226 patients with a baseline value and at least one post-treatment value.
bThe denominator used to calculate the rate for each laboratory parameter varied from 231 to 232 based on the number of patients with a baseline value and at least one post-treatment value.
cNo Grade 4 laboratory abnormalities worsening from baseline were reported.

VISION

The safety of PLUVICTO was evaluated in the VISION study in patients with progressive, PSMA-positive mCRPC previously treated with ARPI therapy and taxane-based chemotherapy [see Clinical Studies (14.2)]. Patients received at least one dose of either PLUVICTO 7.4 GBq (200 mCi) administered every 6 weeks plus BSoC (N = 529) or BSoC alone (N = 205). The median duration of exposure to PLUVICTO plus BSoC was 7.8 months (range, 0.3 to 36.5). Among patients who received PLUVICTO plus BSoC, the median number of doses of PLUVICTO received was 5 (range, 1 to 6). The median cumulative administered activity of PLUVICTO was 37.5 GBq (range, 7.0 to 48.3).

Serious adverse reactions occurred in 37% of patients who received PLUVICTO plus BSoC. Serious adverse reactions in > 1% of patients who received PLUVICTO plus BSoC included musculoskeletal pain (4%), hemorrhage (4%), sepsis (3.2%), urinary tract infection (3%), anemia (2.8%), acute kidney injury (1.9%), pneumonia (1.7%), pyrexia (1.5%), pancytopenia (1.3%), spinal cord compression (1.1%), and pulmonary embolism (1.1%).

Fatal adverse reactions occurred in 3% of patients who received PLUVICTO plus BSoC, including sepsis (0.9%), pancytopenia (0.6%), hepatic failure (0.4%), intracranial hemorrhage (0.2%), subdural hematoma (0.2%), ischemic stroke (0.2%), COVID-19 (0.2%), and aspiration pneumonia (0.2%).

PLUVICTO was permanently discontinued due to adverse reactions in 12% of patients. Adverse reactions leading to permanent discontinuation of PLUVICTO in ≥ 1% of patients who received PLUVICTO plus BSoC were anemia (2.8%), thrombocytopenia (2.8%), and leukopenia (including neutropenia) (1.7%).

Adverse reactions leading to a dose interruption of PLUVICTO occurred in 16% of patients. The most frequent (≥ 3%) adverse reactions leading to a dose interruption of PLUVICTO in patients who received PLUVICTO plus BSoC were anemia (5%) and thrombocytopenia (3.6%).

Adverse reactions leading to a dose reduction of PLUVICTO occurred in 6% of patients. The most frequent (≥ 1%) adverse reactions leading to a dose reduction of PLUVICTO in patients who received PLUVICTO plus BSoC were thrombocytopenia (1.9%) and anemia (1.3%).

Table 5 and Table 6 summarize the incidence of adverse reactions and laboratory abnormalities, respectively, in VISION.

Table 5: Adverse Reactions (≥ 10%) in Patients With PSMA-Positive mCRPC Who Received PLUVICTO Plus BSoC in VISION
Adverse reactions | PLUVICTO plus BSoC (N = 529) |  | BSoC (N = 205)
Adverse reactions | All Grades (%) | Grades 3 or 4 (%) | All Grades (%) | Grades 3 or 4 (%)
General disorders
Fatiguea | 48 | 7 | 29 | 2.4
Decreased appetite | 21 | 1.9 | 15 | 0.5
Weight decreased | 11 | 0.4 | 10 | 0.5
Peripheral edemaa | 10 | 0.4 | 7 | 1
Gastrointestinal disorders
Dry moutha | 39 | 0 | 1 | 0
Nausea | 36 | 1.3 | 17 | 0.5
Constipation | 20 | 1.1 | 11 | 0.5
Vomitinga | 19 | 0.9 | 6 | 0.5
Diarrhea | 19 | 0.8 | 2.9 | 0.5
Abdominal paina | 12 | 1.3 | 6 | 0.5
Musculoskeletal and connective tissue disorders
Back pain | 24 | 3.6 | 15 | 3.9
Arthralgia | 22 | 1.1 | 13 | 0.5
Bone pain | 11 | 2.5 | 8 | 2.4
Renal and urinary disorders
Urinary tract infectiona | 12 | 3.8 | 1 | 0.5
Abbreviation: BSoC, best standard of care.
aIncludes multiple similar terms.

Clinically relevant adverse reactions in < 10% of patients who received PLUVICTO plus BSoC included acute kidney injury, dizziness, dysgeusia, headache, pyrexia, dry eye, oral fungal infection, vertigo, gastroesophageal reflux disease, stomatitis, pancytopenia, dry skin, dysphagia, esophagitis, and bone marrow failure.

Table 6: Select Laboratory Abnormalities (≥ 10%) That Worsened From Baseline in Patients With PSMA-Positive mCRPC Who Received PLUVICTO Plus BSoC (Between Arm Difference of ≥ 5% All Grades) in VISION
Laboratory abnormalities | PLUVICTO plus BSoCa |  | BSoCb
Laboratory abnormalities | All Grades (%) | Grades 3 or 4 (%) | All Grades (%) | Grades 3 or 4 (%)
Hematology
Decreased lymphocytes | 85 | 47 | 51 | 18
Decreased hemoglobin | 64 | 15c | 34 | 7c
Decreased platelets | 45 | 9 | 20 | 2.5
Decreased neutrophils | 28 | 4.7 | 9 | 0.5
Chemistry
Decreased estimated glomerular filtration rate (eGFR) | 43 | 3.6 | 28 | 2.5
Decreased sodium | 34 | 0.6c | 23 | 1
Decreased calcium | 34 | 1.9 | 18 | 1.5
Increased aspartate aminotransferase (AST) | 29 | 1.1 | 18 | 1c
Increased potassium | 24 | 0.6 | 18 | 0.5c
Increased sodium | 11 | 0c | 5 | 0c
Abbreviation: BSoC, best standard of care.
aThe denominator used to calculate the rate for each laboratory parameter varied from 506 to 529 based on the number of patients with a baseline value and at least one post-treatment value.
bThe denominator used to calculate the rate for each laboratory parameter varied from 194 to 198 based on the number of patients with a baseline value and at least one post-treatment value.
cNo Grade 4 laboratory abnormalities worsening from baseline were reported.

8 USE IN SPECIFIC POPULATIONS

8.1 Pregnancy

Risk Summary

The safety and efficacy of PLUVICTO have not been established in females. Based on its mechanism of action, PLUVICTO can cause fetal harm [see Clinical Pharmacology (12.1)]. There are no available data on PLUVICTO use in pregnant females. No animal studies using lutetium Lu 177 vipivotide tetraxetan have been conducted to evaluate its effect on female reproduction and embryo-fetal development; however, all radioactive emissions, including those from PLUVICTO, can cause fetal harm.

8.2 Lactation

Risk Summary

The safety and efficacy of PLUVICTO have not been established in females. There are no data on the presence of lutetium Lu 177 vipivotide tetraxetan in human milk or its effects on the breastfed child or on milk production.

8.3 Females and Males of Reproductive Potential

Contraception

Males

Advise males with female partners of reproductive potential to use effective contraception during treatment with PLUVICTO and for 14 weeks after the last dose [see Clinical Pharmacology (12.1), Nonclinical Toxicology (13.1)].

Infertility

The recommended cumulative dose of 44.4 GBq of PLUVICTO results in a radiation absorbed dose to the testes within the range where PLUVICTO may cause temporary or permanent infertility.

8.4 Pediatric Use

The safety and effectiveness of PLUVICTO in pediatric patients have not been established.

8.5 Geriatric Use

Of the 227 patients who received at least one dose of PLUVICTO in the PSMAfore study, 177 patients (78%) were 65 years of age or older and 83 patients (37%) were 75 years of age or older. No overall differences in effectiveness were observed between patients ≥ 75 years of age and younger patients. Serious adverse reactions occurred in 20% of patients ≥ 75 years of age and in 20% of younger patients. Grade ≥ 3 adverse reactions occurred in 39% of patients ≥ 75 years of age and in 34% of younger patients.

Of the 529 patients who received at least one dose of PLUVICTO plus BSoC in the VISION study, 387 patients (73%) were 65 years of age or older and 143 patients (27%) were 75 years of age or older. No overall differences in effectiveness were observed between patients ≥ 75 years of age and younger patients. Serious adverse reactions occurred in 41% of patients ≥ 75 years of age and in 35% of younger patients. Grade ≥ 3 adverse reactions occurred in 56% of patients ≥ 75 years of age and in 53% of younger patients.

8.6 Renal Impairment

Exposure of lutetium Lu 177 vipivotide tetraxetan is expected to increase with the degree of renal impairment [see Clinical Pharmacology (12.3)]. No dose adjustment is recommended for patients with mild (baseline CLcr 60 to 89 mL/min by Cockcroft-Gault) to moderate (CLcr 30 to 59 mL/min) renal impairment; however, patients with mild to moderate renal impairment may be at greater risk of toxicity. Frequently monitor renal function and adverse reactions in patients with mild to moderate renal impairment [see Dosage and Administration (2.4)]. The pharmacokinetics and safety of PLUVICTO have not been studied in patients with severe (CLcr 15 to 29 mL/min) renal impairment or end-stage renal disease.

10 OVERDOSAGE

In the event of administration of a radiation overdosage with PLUVICTO, reduce the radiation absorbed dose to the patient by increasing the elimination of the radionuclide from the body by frequent micturition or by forced diuresis and frequent bladder voiding. Estimate the effective radiation dose that was applied and treat with additional supportive care measures as clinically indicated.

11 DESCRIPTION

PLUVICTO (lutetium Lu 177 vipivotide tetraxetan) is a radioligand therapeutic agent. Lutetium Lu 177 vipivotide tetraxetan is a PSMA-binding ligand bound to a DOTA chelator radiolabeled with lutetium-177.

The chemical name is 2-[4-[2-[[4-[[(2S)-1-[[(5S)-5-carboxy-5-[[(1S)-1,3-dicarboxy propyl]carbamoylamino]pentyl]amino]-3-naphthalen-2-yl-1-oxopropan-2-yl]carbamoyl]cyclohexyl]methylamino]-2-oxoethyl]-4,7,10-tris(carboxylatomethyl)-1,4,7,10-tetrazacyclododec-1-yl]acetate; lutetium-177(3+). The molecular mass is 1216.06 g/mol and the molecular formula is C49H68^177LuN9O16. The chemical structure for lutetium Lu 177 vipivotide tetraxetan is shown below:

PLUVICTO (lutetium Lu 177 vipivotide tetraxetan) 1,000 MBq/mL (27 mCi/mL) Injection is supplied as a sterile, clear, colorless to slightly yellow solution for intravenous use. Each single-dose vial contains acetic acid (0.30 mg/mL), sodium acetate (0.41 mg/mL), gentisic acid (0.39 mg/mL), sodium ascorbate (50.0 mg/mL), pentetic acid (0.10 mg/mL), and water for injection (q.s. to 1 mL). The pH range of the solution is 4.5 to 7.0.

11.1 Physical Characteristics

Lutetium-177 decays to a stable hafnium-177 with a physical half-life of 6.647 days by emitting beta-minus radiation with a maximum energy of 498 keV (79%) and photonic radiation (γ) of 208 keV (11%) and 113 keV (6.4%).

The main radiations of lutetium-177 are detailed in Table 7.

Table 7: Lutetium-177 Main Radiations
Radiation | Energy (keV) | Iβ^-% | Iγ%
β^- | 176.5 | 12.2
β^- | 248.1 | 0.05
β^- | 384.9 | 9.1
β^- | 497.8 | 78.6
γ | 71.6 |  | 0.15
γ | 112.9 |  | 6.40
γ | 136.7 |  | 0.05
γ | 208.4 |  | 11.0
γ | 249.7 |  | 0.21
γ | 321.3 |  | 0.22

11.2 External Radiation

Table 8 summarizes the radioactive decay properties of lutetium-177.

Table 8: Physical Decay Chart: Lutetium-177 Physical Half-life = 6.647 days
Hours | Fraction remaining
0 | 1.000
1 | 0.996
2 | 0.991
5 | 0.979
10 | 0.958
24 (1 day) | 0.901
48 (2 days) | 0.812
72 (3 days) | 0.731
120 (5 days) | 0.594
168 (7 days) | 0.482
336 (14 days) | 0.232
720 (30 days) | 0.044
1080 (45 days) | 0.009

12 CLINICAL PHARMACOLOGY

12.1 Mechanism of Action

Lutetium Lu 177 vipivotide tetraxetan is a radioligand therapeutic agent. The active moiety of lutetium Lu 177 vipivotide tetraxetan is the radionuclide lutetium-177 which is linked to a moiety that binds to PSMA, a transmembrane protein that is expressed in prostate cancer, including mCRPC. Upon binding of lutetium Lu 177 vipivotide tetraxetan to PSMA-expressing cells, the beta-minus emission from lutetium-177 delivers radiation to PSMA-expressing cells, as well as to surrounding cells, and induces DNA damage which can lead to cell death.

12.2 Pharmacodynamics

Lutetium Lu 177 vipivotide tetraxetan exposure-efficacy relationships and the time course of pharmacodynamic response have not been fully characterized.

Cardiac Electrophysiology

At the recommended dosage, PLUVICTO does not cause large mean increases (> 20 ms) in the QTc interval.

12.3 Pharmacokinetics

Pharmacokinetics of lutetium Lu 177 vipivotide tetraxetan are expressed as geometric mean (geometric mean coefficient of variation) unless otherwise specified.

The blood lutetium Lu 177 vipivotide tetraxetan area under the curve (AUC) is 52.3 ng.h/mL (31.4%) and the maximum blood concentration (Cmax) is 6.58 ng/mL (43.5%) at the recommended dosage.

Distribution

Lutetium Lu 177 vipivotide tetraxetan volume of distribution is 123 L (78.1%).

Within 2.5 hours after administration, lutetium Lu 177 vipivotide tetraxetan distributes in gastrointestinal tract, liver, lungs, kidneys, heart wall, bone marrow, and salivary glands.

Vipivotide tetraxetan and non-radioactive lutetium vipivotide tetraxetan are 60% to 70% bound to human plasma proteins.

Elimination

The lutetium Lu 177 vipivotide tetraxetan terminal elimination half-life is 41.6 hours (68.8%) and the clearance (CL) is 2.04 L/h (31.5%).

Metabolism

Lutetium Lu 177 vipivotide tetraxetan does not undergo hepatic or renal metabolism.

Excretion

Lutetium Lu 177 vipivotide tetraxetan is primarily eliminated renally.

Specific Populations

Exposure (AUC) of lutetium Lu 177 vipivotide tetraxetan increased with decreasing creatinine clearance (CLcr). The effect of baseline CLcr < 54 mL/min on lutetium Lu 177 vipivotide tetraxetan pharmacokinetics has not been studied.

Drug Interaction Studies

In Vitro Studies

CYP450 enzymes: Vipivotide tetraxetan is not a substrate of cytochrome P450 (CYP450) enzymes. Vipivotide tetraxetan did not induce CYP1A2, 2B6 or 3A4; and did not inhibit CYP1A2, 2B6, 2C8, 2C9, 2C19, 2D6 or 3A in vitro.

Transporters: Vipivotide tetraxetan is not a substrate of BCRP, P-gp, MATE1, MATE2-K, OAT1, OAT3 or OCT2. Vipivotide tetraxetan did not inhibit BCRP, P-gp, MATE1, MATE2-K, OAT1, OAT3, OATP1B1, OATP1B3, OCT1 or OCT2 in vitro.

13 NONCLINICAL TOXICOLOGY

13.1 Carcinogenesis, Mutagenesis, Impairment of Fertility

Carcinogenicity and mutagenicity studies have not been conducted with lutetium Lu 177 vipivotide tetraxetan; however, radiation is a carcinogen and mutagen.

No animal studies were conducted to determine the effects of lutetium Lu 177 vipivotide tetraxetan on fertility.

14 CLINICAL STUDIES

14.1 PSMA-Positive mCRPC Previously Treated With ARPI Therapy

PSMAfore

The efficacy of PLUVICTO was evaluated in PSMAfore (NCT04689828), a randomized (1:1), multicenter, open-label trial that evaluated PLUVICTO (N = 234) versus a change in ARPI (N = 234) in patients with progressive, PSMA-positive mCRPC. Randomization was stratified by setting of prior ARPI use [castration-resistant prostate cancer (CRPC) vs. hormone-sensitive prostate cancer (HSPC)] and by symptomatology [asymptomatic or mildly symptomatic vs. symptomatic]. Patients were required to have a castrate level of serum/plasma testosterone by either medical castration or prior orchiectomy at study entry. Patients were required to have progressed only once on an ARPI (abiraterone acetate, enzalutamide, darolutamide, or apalutamide). Prior taxane-based chemotherapy was only allowed in the adjuvant or neoadjuvant setting greater than 12 months before enrollment. Patients were considered appropriate for delay of taxane-based chemotherapy by the investigator. Patients were required to have PSMA-positive mCRPC defined as having at least one tumor lesion (soft tissue or bone) with gallium Ga 68 gozetotide uptake greater than in normal liver. Patients were considered ineligible if any intraprostatic lesion or any one lesion larger than size criteria [organs ≥ 1 cm in longest diameter, lymph nodes ≥ 2.5 cm in short axis, bones (soft tissue component) ≥ 1 cm in longest diameter] had gallium Ga 68 gozetotide uptake less than or equal to uptake in normal liver.

Patients received PLUVICTO 7.4 GBq (200 mCi) every 6 weeks for 6 doses or a change in ARPI. Supportive care administered at the investigator’s discretion included bone-targeted agents; androgen deprivation therapy (ADT); or palliative radiotherapy.

The median age was 72 years (range, 43 to 94 years); 91% were White; 2.6% Black or African American; 0.6% Asian; 6% were Hispanic or Latino; 99% had ECOG PS0-1.

The major efficacy outcome measure was radiographic progression-free survival (rPFS) as determined by blinded independent central review (BICR) per Prostate Cancer Working Group 3 (PCWG3)-modified Response Evaluation Criteria in Solid Tumors (RECIST) v1.1 criteria. Additional efficacy outcome measures were Overall Survival (OS) and Overall Response Rate (ORR).

PSMAfore demonstrated a statistically significant improvement in rPFS for PLUVICTO compared to a change in ARPI.

Of patients that were randomized to receive a change in ARPI, 141 patients (60%) crossed over to receive PLUVICTO after confirmation of radiographic disease progression by BICR.

Efficacy results for PSMAfore are presented in Table 9 and Figure 1.

Table 9: Efficacy Results in PSMAfore
 | PLUVICTO | ARPI
Radiographic progression-free survival (rPFS)a | N = 233b | N = 234
Events (progression or death), n (%) | 60 (26) | 106 (45)
Median, months (95% CI)c | 9.3 (7, NE) | 5.6 (4, 6)
Hazard ratio (95% CI)d | 0.41 (0.29, 0.56)
P-valuee | < 0.0001
Overall survival (OS) | N = 234 | N = 234
Deaths, n (%) | 142 (61) | 157 (67)
Median, months (95% CI)c | 24.5 (19.5, 28.9) | 23.1 (19.6, 25.5)
Hazard ratio (95% CI)d | 0.91 (0.72, 1.14)
P-valuee | NS
Overall response rate (ORR)a,f
Patients with measurable disease at baseline | N = 72 | N = 72
ORR (CR + PR), n (%) (95% CI) | 35 (49) (37, 61) | 10 (14) (7, 24)
Complete response (CR), n (%) | 15 (21) | 2 (2.8)
Partial response (PR), n (%) | 20 (28) | 8 (11)
ARPI = androgen receptor pathway inhibitor; NE = Not estimable; NS = Not statistically significant
aBy BICR per PCWG3-modified RECIST v1.1 criteria.
bExcludes one patient in the PLUVICTO arm who was randomized after the data cut-off for the rPFS primary analysis.
cBased on Kaplan-Meier estimate.
dHazard ratio based on the stratified Cox PH model.
eStratified log-rank test one-sided p-value.
fResponses are based on soft tissue and bone lesion assessment.

Figure 1. Kaplan-Meier Plot of Radiographic Progression-Free Survival in PSMAfore

14.2 PSMA-Positive mCRPC Previously Treated With ARPI Therapy and Taxane-Based Chemotherapy

VISION

The efficacy of PLUVICTO was evaluated in VISION (NCT03511664), a randomized (2:1), multicenter, open-label trial of PLUVICTO plus BSoC (N = 551) versus BSoC alone (N = 280) in patients with progressive, PSMA-positive mCRPC. Randomization was stratified by baseline lactase dehydrogenase (LDH ≤ 260 IU/L vs. > 260 IU/L), presence of liver metastases (yes vs. no), ECOG PS score (0 or 1 vs. 2), and inclusion of an AR pathway inhibitor as part of BSoC (yes vs. no) at the time of randomization. Patients were required to have a castrate level of serum/plasma testosterone by either medical castration or prior orchiectomy at study entry. Patients were required to have received at least one ARPI, and 1 or 2 prior taxane-based chemotherapy regimens. Eligible patients were required to have PSMA-positive mCRPC defined as having at least one tumor lesion (soft tissue or bone) with gallium Ga 68 gozetotide uptake greater than in normal liver. Patients were considered ineligible if any one lesion larger than size criteria [organs ≥ 1 cm in short axis, lymph nodes ≥ 2.5 cm in short axis, bones (soft tissue component) ≥ 1 cm in short axis] had gallium Ga 68 gozetotide uptake less than or equal to uptake in normal liver.

Patients received PLUVICTO 7.4 GBq (200 mCi) every 6 weeks for up to a total of 6 doses plus BSoC or BSoC alone. BSoC administered at the investigator’s discretion included ketoconazole; radiation therapy to localized prostate cancer targets; bone-targeted agents; ADT; ARPIs. Patients continued treatment for up to 4-6 doses, or until disease progression or unacceptable toxicity. Patients with stable disease or partial response after 4 doses of PLUVICTO plus BSoC received up to 2 additional doses per investigator’s discretion.

The median age was 71 years (range, 40 to 94 years); 87% White; 7% Black or African American; 2.4% Asian; 1.7% were Hispanic or Latino; 92% had ECOG PS0-1; 8% had ECOG PS2. All patients had received at least one prior taxane-based chemotherapy regimen and 41% of patients received two. One prior ARPI had been administered to 51% of patients, 41% of patients had received 2, and 8% of patients had received 3 or more. During the treatment period, 53% of patients in the PLUVICTO plus BSoC arm and 68% of patients in the BSoC alone arm received at least one ARPI.

The major efficacy outcome measures were OS and rPFS as determined by BICR per PCWG3-modified RECIST v1.1 criteria. An additional efficacy outcome measure was ORR.

VISION demonstrated a statistically significant improvement in both major efficacy outcome measures of OS and rPFS by BICR with PLUVICTO plus BSoC compared to treatment with BSoC alone. Interpretation of the magnitude of the rPFS effect was limited due to a high degree of censoring from early drop out in the control arm.

Efficacy results for VISION are presented in Table 10 and Figure 2.

Table 10: Efficacy Results in VISION
 | PLUVICTO plus BSoC | BSoC
Overall survival (OS) | N = 551 | N = 280
Deaths, n (%) | 343 (62) | 187 (67)
Median, months (95% CI)a | 15.3 (14.2, 16.9) | 11.3 (9.8, 13.5)
Hazard ratio (95% CI)b | 0.62 (0.52, 0.74)
P-valuec | < 0.001
Overall response rate (ORR)d,e
Patients with measurable disease at baseline | N = 184 | N = 64
ORR (CR + PR), n (%) (95% CI) | 91 (49) (42, 57) | 1 (1.6) (0, 8)
Complete response (CR), n (%) | 17 (9) | 0 (0)
Partial response (PR), n (%) | 74 (40) | 1 (1.6)
P-valuef | < 0.001
aBased on Kaplan-Meier estimate.
bHazard ratio based on the stratified Cox PH model.
cStratified log-rank test two-sided p-value.
dResponses are based on soft tissue and bone lesion assessment.
eBy BICR per PCWG3-modified RECIST v1.1 criteria.
fStratified Wald’s Chi-square test two-sided p-value.

Figure 2. Kaplan-Meier Plot of Overall Survival in VISION

16 HOW SUPPLIED/STORAGE AND HANDLING

PLUVICTO Injection containing 1,000 MBq/mL (27 mCi/mL) of lutetium Lu 177 vipivotide tetraxetan is a sterile, preservative-free and clear, colorless to slightly yellow solution for intravenous use supplied in a clear, colorless Type I glass 30 mL single-dose vial containing 7.4 GBq (200 mCi) ± 10% of lutetium Lu 177 vipivotide tetraxetan at the date and time of administration (NDC# 0078-1217-61). The solution volume in the vial can range from 7.5 mL to 12.5 mL in order to provide a total of 7.4 GBq (200 mCi) of radioactivity at the date and time of administration.

The product vial is enclosed within a lead shielded container (NDC# 0078-1217-61) for protective shielding and placed in a plastic sealed container. The product is shipped in a Type A package.

The shelf life is 120 hours (5 days) from the date and time of calibration.

Store below 30°C (86°F). Do not freeze. Store in the original package to protect from ionizing radiation (lead shielding).

Store PLUVICTO in accordance with local and federal laws on radioactive materials.

Do not use PLUVICTO after the expiration date and time which are stated on the label.

Dispose of any unused medicinal product or waste material in accordance with local and federal laws.

Lutetium-177 for PLUVICTO may be prepared using two different sources of stable nuclides (either lutetium-176 or ytterbium-176) that require different waste management. Lutetium-177 for PLUVICTO is prepared using ytterbium-176 (“non-carrier added”) unless otherwise communicated on the product batch release certificate.

17 PATIENT COUNSELING INFORMATION

Risk From Radiation Exposure

Ensure patients increase oral fluid intake and advise patients to void as often as possible to reduce bladder radiation.

Before the patient is released, inform patients about the necessary radioprotection precautions to follow to minimize radiation exposure to others.

After each administration of PLUVICTO, advise patients to:

- Limit close contact (less than 3 feet) with others for 2 days or with children and pregnant women for 7 days.
- Refrain from sexual activity for 7 days.
- Sleep in a separate room from others for 3 days, from children for 7 days, or from pregnant women for 15 days [see Warnings and Precautions (5.1)].

Myelosuppression

Advise patients to contact their healthcare provider for any signs or symptoms of myelosuppression, such as tiredness, weakness, pale skin, shortness of breath, bleeding or bruising more easily than normal or difficulty to stop bleeding, or frequent infections with signs, such as fever, chills, sore throat or mouth ulcers [see Warnings and Precautions (5.2)].

Renal Toxicity

Advise patients to remain well hydrated and to urinate frequently before and after administration of PLUVICTO. Advise patients to contact their healthcare provider for any signs or symptoms of renal toxicity, such as passing urine less often than usual or passing much smaller amounts of urine than usual [see Warnings and Precautions (5.3)].

Embryo-Fetal Toxicity

Advise males that PLUVICTO can cause fetal harm [see Warnings and Precautions (5.4), Use in Specific Populations (8.1)].

Advise male patients with female partners of reproductive potential to use effective contraception during treatment with PLUVICTO and for 14 weeks after the last dose [see Warnings and Precautions (5.4), Use in Specific Populations (8.1, 8.3)].

Infertility

Advise males of reproductive potential that PLUVICTO may cause temporary or permanent infertility [see Warnings and Precautions (5.5), Use in Specific Populations (8.3)].

Distributed by:
Novartis Pharmaceuticals Corporation
East Hanover, NJ 07936

©2025 Novartis

PLUVICTO® is a registered trademark of Novartis AG and/or its affiliates.

U.S. Patents 10398791; 10406240; 11318121; 12208102

T2025-31

PRINCIPAL DISPLAY PANEL

PLUVICTO®

1,000 MBq/mL (27 mCi/mL)

lutetium Lu 177 vipivotide tetraxetan injection

Intravenous use Single-dose vial

Sterile

NDC# 0078-1217-61

Rx Only

NOVARTIS